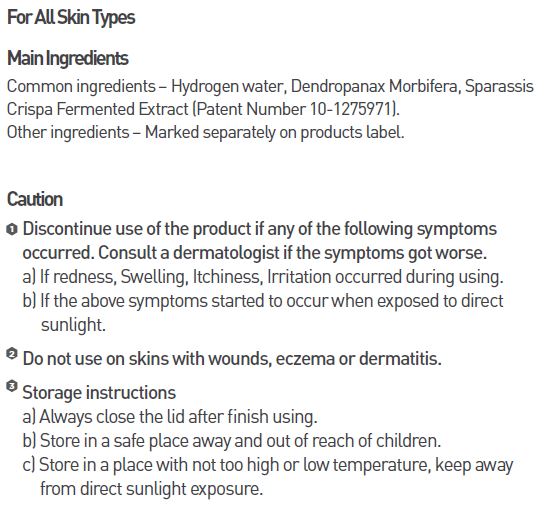 DRUG LABEL: MEDI HYDRO DP STEM C AMPOULE
NDC: 70694-0008 | Form: LIQUID
Manufacturer: Inc MBG
Category: otc | Type: HUMAN OTC DRUG LABEL
Date: 20190124

ACTIVE INGREDIENTS: GLYCERIN 10 g/100 mL
INACTIVE INGREDIENTS: WATER; BUTYLENE GLYCOL

INDICATIONS AND USAGE

Open the lid, press the lid to fill the dropper and apply evenly 3-4 drops to the desired parts, gently tap with the fingers to allow it to absorb

Keep out of reach of children.

DOSAGE AND ADMINISTRATION

for external use only

WARNINGS

Discontinue use of the product if any of the following symptoms occurred. Consult a dermatologist if the symptoms got worse.
a) If redness, Swelling, Itchiness, Irritation occurred during using.
b) If the above symptoms started to occur when exposed to direct sunlight.
Do not use on skins with wounds, eczema or dermatitis.

Storage instructions
a) Always close the lid after finish using.
b) Store in a safe place away and out of reach of children.
c) Store in a place with not too high or low temperature, keep awayfrom direct sunlight exposure.

PURPOSE

Ampoule with human stem-cell-culture fluids and EGF that helps improving skin texture

INACTIVE INGREDIENT

water, butylene glycol, hyaluronic acid, alcohol, etc.

ACTIVE INGREDIENT

glycerin